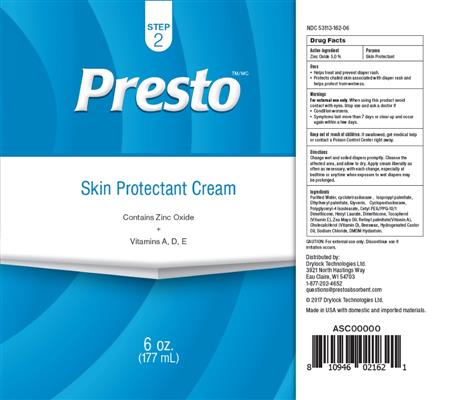 DRUG LABEL: PRESTO
NDC: 53113-162 | Form: CREAM
Manufacturer: GADAL Laboratories, Inc
Category: otc | Type: HUMAN OTC DRUG LABEL
Date: 20171215

ACTIVE INGREDIENTS: ZINC OXIDE 5 g/1 mL
INACTIVE INGREDIENTS: APIS CERANA WORKER SECRETION; CETYL PEG/PPG-10/1 DIMETHICONE (HLB 1.5); CHOLECALCIFEROL; CORN OIL; CYCLOMETHICONE 4; CYCLOMETHICONE 5; HYDROGENATED CASTOR OIL; DIMETHICONE; DMDM HYDANTOIN; ETHYLHEXYL PALMITATE; GLYCERIN; HEXYL LAURATE; ISOPROPYL PALMITATE; SODIUM CHLORIDE; TOCOPHEROL; VITAMIN A PALMITATE; WATER

ACTIVE INGREDIENT

Active ingredient | Purpose
Zinc Oxide 5.0 % | Skin Protectant

INACTIVE INGREDIENT

Purified Water, cyclotetrasiloxane , Isopropyl palmitate,
Ethylhexyl palmitate, Glycerin, Cyclopentasiloxane,
Polyglyceryl-4 Isostearate, Cetyl PEG/PPG-10/1
Dimethicone, Hexyl Laurate, Dimethicone, Tocopherol
(Vitamin E), Zea Mays Oil, Retinyl palmitate(Vitamin A),
Cholecalciferol (Vitamin D), Beeswax, Hydrogenated Castor
Oil, Sodium Chloride, DMDM Hydantoin.

KEEP OUT OF REACH OF CHILDREN

If swallowed, get medical help or contact a Poison Control Center right away.

INDICATIONS & USAGE

Helps treat and prevent diaper rash.

WARNINGS

For external use only. When using this product avoid contact with eyes. Stop use and ask a doctor if
• Condition worsens.
• Symptoms last more than 7 days or clear up and occur again within a few days.

DOSAGE & ADMINISTRATION

Change wet and soiled diapers promptly. Cleanse the affected area, and allow to dry. Apply cream liberally as often as necessary, with each change, especially at bedtime or anytime when exposure to wet diapers may be prolonged.

PURPOSE

• Helps treat and prevent diaper rash.
• Protects chafed skin associated with diaper rash and helps protect from wetness.

PRESTO

Distributed by:
Drylock Technologies Ltd.
3921 North Hastings Way
Eau Claire, WI 54703
1-877-202-4652
questions@prestoabsorbent.com
© 2017 Drylock Technologies Ltd.
Made in USA with domestic and imported materials.